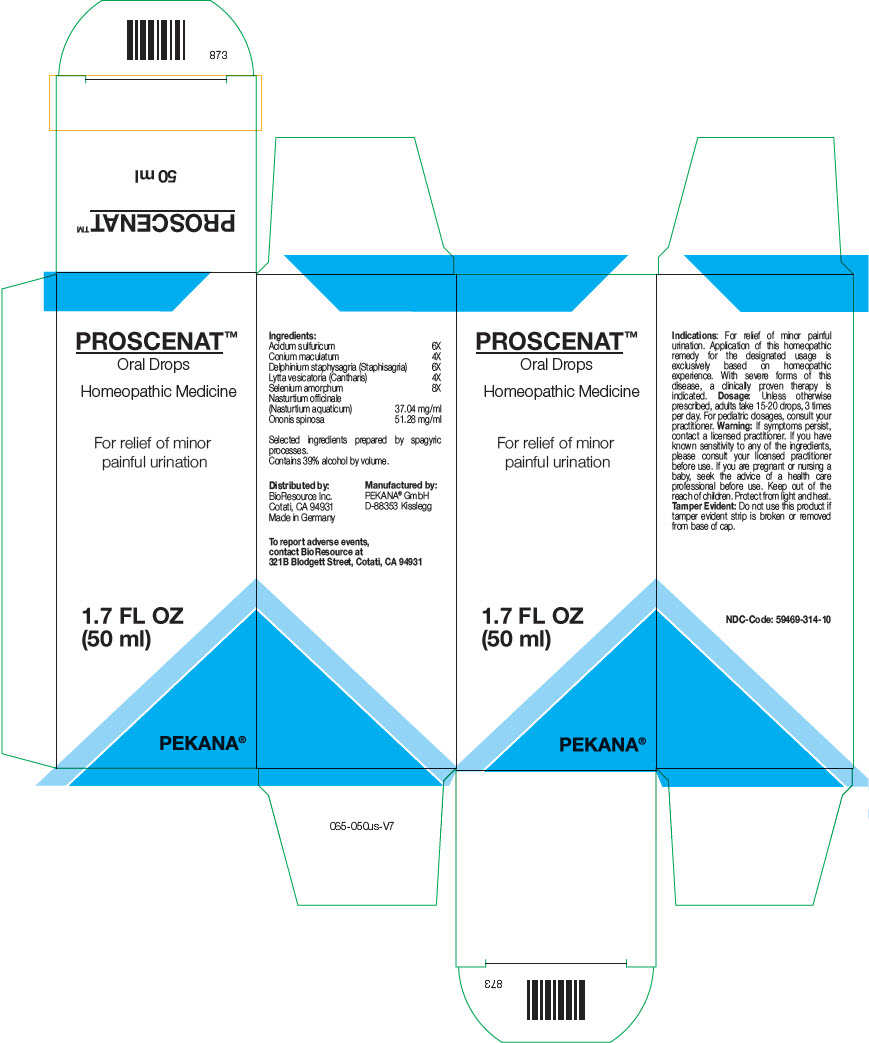 DRUG LABEL: PROSCENAT
NDC: 59469-314 | Form: SOLUTION/ DROPS
Manufacturer: PEKANA Naturheilmittel GmbH
Category: homeopathic | Type: HUMAN OTC DRUG LABEL
Date: 20230111

ACTIVE INGREDIENTS: SULFURIC ACID 6 [hp_X]/50 mL; LYTTA VESICATORIA 4 [hp_X]/50 mL; CONIUM MACULATUM FLOWERING TOP 4 [hp_X]/50 mL; SELENIUM 8 [hp_X]/50 mL; DELPHINIUM STAPHISAGRIA SEED 6 [hp_X]/50 mL; NASTURTIUM OFFICINALE WHOLE 1852 mg/50 mL; ONONIS SPINOSA WHOLE 2564 mg/50 mL
INACTIVE INGREDIENTS: WATER; ALCOHOL

PROSCENAT™

ACTIVE INGREDIENT

Ingredients:
Acidum sulfuricum | 6X
Conium maculatum | 4X
Delphinium staphysagria (Staphisagria) | 6X
Lytta vesicatoria (Cantharis) | 4X
Selenium amorphum | 8X
Nasturtium officinale (Nasturtium aquaticum) | 37.04 mg/ml
Ononis spinosa | 51.28 mg/ml

Selected ingredients prepared by spagyric processes.

INACTIVE INGREDIENT

Contains 39% alcohol by volume.

Indications

PURPOSE

For relief of minor painful urination. Application of this homeopathic remedy for the designated usage is exclusively based on homeopathic experience. With severe forms of this disease, a clinically proven therapy is indicated.

Dosage

Unless otherwise prescribed, adults take 15-20 drops, 3 times per day. For pediatric dosages, consult your practitioner.

Warning

If symptoms persist, contact a licensed practitioner. If you have known sensitivity to any of the ingredients, please consult your licensed practitioner before use. If you are pregnant or nursing a baby, seek the advice of a health care professional before use.

Keep out of the reach of children.

STORAGE AND HANDLING

Protect from light and heat.

Tamper Evident

Do not use this product if tamper evident strip is broken or removed from base of cap.

QUESTIONS

To report adverse events, contact BioResource at 321B Blodgett Street, Cotati, CA 94931

Distributed by:
BioResource Inc.
Cotati, CA 94931

Manufactured by:
PEKANA® GmbH
D-88353 Kisslegg

PRINCIPAL DISPLAY PANEL - 50 ml Bottle Box

PROSCENAT™
Oral Drops

Homeopathic Medicine

For relief of minor
painful urination

1.7 FL OZ
(50 ml)

PEKANA®